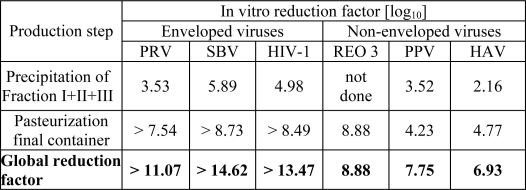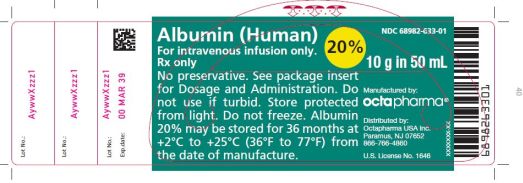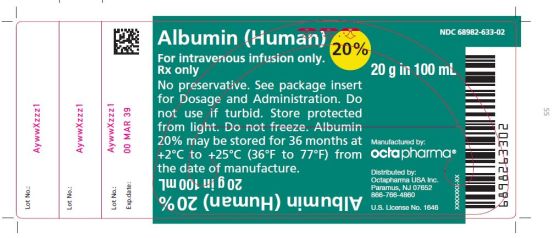 DRUG LABEL: Albumin (Human)
NDC: 68982-633 | Form: SOLUTION
Manufacturer: Octapharma USA Inc
Category: other | Type: PLASMA DERIVATIVE
Date: 20200406

ACTIVE INGREDIENTS: ALBUMIN HUMAN 200 g/1000 mL

HIGHLIGHTS OF PRESCRIBING INFORMATION

These highlights do not include all the information needed to use ALBUMIN (HUMAN) 20% safely and effectively. See full prescribing information for ALBUMIN (HUMAN) 20%.
ALBUMIN (HUMAN) 20% for infusion, for intravenous use
Initial U.S. Approval: 2006

1 INDICATIONS AND USAGE

ALBUMIN (HUMAN) 20% is indicated for the restoration and maintenance of circulating blood volume for:

Hypovolemia. (1.1)

Hypoalbuminemia. (1.2)

Prevention of central volume depletion after paracentesis due to cirrhotic ascites. (1.3)

Ovarian hyperstimulation syndrome (OHSS). (1.4)

Adult respiratory distress syndrome (ARDS). (1.5)

Acute nephrosis. (1.6)

Hemolytic Disease of the Newborn (HDN). (1.7)

2 DOSAGE AND ADMINISTRATION

Intravenous use only.

Daily dose should not exceed 2 g per kg body weight. (2.1)

Indication | Dose
Hypovolemia | Adults: 25 g (2.1) Children (less than 13 years): 2.5 to 1.25 g (2.1)
Hypoalbuminemia | Adults: 50 to 75 g (2.1)
Prevention of volume depletion after paracentesis | Adults: 8 g for every 1,000 mL of ascitic fluid removed (2.1)
Ovarian hyperstimulation syndrome | Adults: 50 to 100 g over 4 hours and repeated at 4-12 hour intervals as necessary (2.1)
Adult respiratory distress syndrome | Adults: 25 g over 30 minutes and repeated at 8 hours for 3 days, if necessary (2.1)
Acute nephrosis | Adults: 25 g together with diuretic once a day for 7-10 days (2.1)
Hemolytic Disease of the Newborn | 1 g per kilogram body weight prior or during exchange transfusion (2.1)

Do not dilute with sterile water for injection as this may cause hemolysis in recipients. (5.6)

Store protected from light. (16)

Do not freeze. (16)

If large volumes (> 1500 ml) are administered, warm the product to room temperature before use. (2.2)

Bottles are for single use only. (2.2)

3 DOSAGE FORMS AND STRENGTHS

10 g in 50 mL infusion bottle (3)

20 g in 100 mL infusion bottle (3)

4 CONTRAINDICATIONS

Do not use in individuals who are hypersensitive to albumin preparations, any ingredient in the formulation, or components of the container. (4)

5 WARNINGS AND PRECAUTIONS

Hypersensitivity or allergic reactions have been observed, and may in some cases progress to severe anaphylaxis. Epinephrine should be available immediately to treat any acute hypersensitivity reaction. (5.1)

Hypervolemia: Use with caution in patients who are at risk of hypervolemia or hemodilution. Stop infusion if signs of cardiovascular overload occur. (5.2)

Electrolyte imbalances have been observed. Monitor electrolyte status. (5.3)

Ensure adequate substitution of other blood constituents. Monitor coagulation status and hematocrit. (5.4)

Hypotension has been observed. Monitor hemodynamic performance. (5.5)

Do not dilute solution with sterile water for injection. (5.6)

This product is made from human plasma and may contain infectious agents, e.g., viruses and, theoretically, the Creutzfeldt-Jakob disease agent. (5.7)

6 ADVERSE REACTIONS

Most common adverse reactions seen in clinical trials (≥ 5% incidence) were anaphylactoid type reactions.

To report SUSPECTED ADVERSE REACTIONS, contact Octapharma USA Inc. at phone # 866-766-4860 and/or FDA at 1-800-FDA-1088 or www.fda.gov/medwatch.

8 USE IN SPECIFIC POPULATIONS

Pediatric use: The product should only be administered to pediatric patients if needed. (8.4)

_______________________________________________________________________________________________________________________________________

FULL PRESCRIBING INFORMATION

1 INDICATIONS AND USAGE

1.1 Hypovolemia

ALBUMIN (HUMAN) 20% is indicated in the emergency treatment of hypovolemia with or without shock. Its effectiveness in reversing hypovolemia depends largely upon its ability to draw interstitial fluid into the circulation. It is most effective in patients who are well hydrated. When blood volume deficit is the result of hemorrhage, compatible red blood cells or whole blood should be administered as quickly as possible. [ 1 , 2 ]

When hypovolemia is long standing and hypoalbuminemia exists accompanied by adequate hydration or edema, 20% - 25% albumin solutions should be used. [ 1 ]

1.2 Hypoalbuminemia

For subjects with hypoalbuminemia who are critically ill and/or are bleeding actively, ALBUMIN (HUMAN) 20% infusions may be indicated. [ 3 ] When albumin deficit is the result of excessive protein loss, the effect of administration of ALBUMIN (HUMAN) 20% will be temporary unless the underlying disorder is reversed.

1.3 Prevention of Central Volume Depletion after Paracentesis due to Cirrhotic Ascites (Treatment Adjunct)

ALBUMIN (HUMAN) 20% may be used to maintain cardiovascular function following the removal of large volumes of ascitic fluid after paracentesis due to cirrhotic ascites. [ 2 ]

1.4 Ovarian Hyperstimulation Syndrome (OHSS)

ALBUMIN (HUMAN) 20% may be used as a plasma expander in fluid management relating to severe forms of ovarian hyperstimulation syndrome (OHSS). [7, 8]

1.5 Adult Respiratory Distress Syndrome (ARDS) (Treatment Adjunct)

ALBUMIN (HUMAN) 20% infusions may be indicated in conjunction with diuretics to correct the fluid volume overload associated with ARDS. [ 5 ]

1.6 Acute Nephrosis (Treatment Adjunct)

ALBUMIN (HUMAN) 20% may be used to treat edema in patients with acute nephrosis who are refractory to cyclophosphamide and corticosteroid therapy. [ 1 ]

1.7 Hemolytic Disease of the Newborn (HDN)

ALBUMIN (HUMAN) 20% is indicated in the treatment of hyperbilirubinemia. It may be used prior to or during an exchange procedure in an attempt to bind free and to enhance its removal. [ 6 ]

2 DOSAGE AND ADMINISTRATION

2.1 Dosage

General Recommendations

The concentration of the albumin preparation, dosage and the infusion rate should be adjusted to the patient’s individual requirements.

The dose required depends on the body weight of the patient, the severity of trauma or illness and on continuing fluid and protein losses. Measures of adequacy of circulating volume and not plasma albumin levels should be used to determine the dose required.

The daily dose should not exceed 2 g of ALBUMIN (HUMAN) 20% per kg of body weight.

Hypovolemia

In adults, an intravenous infusion of 25 g should be given. If adequate response (stabilization of circulation) is not achieved within 15 to 30 minutes, an additional dose may be given.

In spite of limited information about the efficacy in pediatric subjects, an intravenous infusion of 2.5 to 12.5 g or 0.5 to 1 g/kg body weight may be given. If adequate response (stabilization of circulation) is not achieved within 15 to 30 minutes, an additional dose may be given.

Hemodilution may follow administration of ALBUMIN (HUMAN) 20%. If hemorrhage has occurred, this may result in relative anemia. This condition should be controlled by the supplemental administration of compatible red blood cells or compatible whole blood.

Hypoalbuminemia

In adults, intravenous infusion of 50 to 75 g of ALBUMIN (HUMAN) 20% may be used. Hypoalbuminemia is usually accompanied by a hidden extravascular albumin deficiency of equal magnitude. This total body albumin deficit must be considered when determining the amount of albumin necessary to reverse the hypoalbuminemia.

In burns, therapy usually starts with the administration of large volumes of crystalloid injection to maintain plasma volume. After 24 hours, ALBUMIN (HUMAN) 20% may be added at an initial dose of 25 g with the dose adjusted thereafter to maintain a plasma protein concentration of 2.5 g per 100 mL or a serum protein concentration of 5.2 g/100 mL.

Prevention of Central Volume Depletion after Paracentesis due to Cirrhotic Ascites

In adults, intravenous infusion of 8 g of ALBUMIN (HUMAN) 20% may be given for every 1,000 mL of ascitic fluid removed.

Ovarian Hyperstimulation Syndrome

In adults, as a guideline, doses of 50 – 100 g of ALBUMIN (HUMAN) 20% should be infused over 4 hours and repeated at 4- to 12-hour intervals as necessary, when infusion of normal saline fails to achieve or maintain hemodynamic stability and urine output. [ 7 ]

Adult Respiratory Distress Syndrome (ARDS)

In adults, a dose of 25 g of ALBUMIN (HUMAN) 20% can be infused over 30 minutes and repeated at 8 hour intervals for 3 days, if necessary. [ 5 ]

Induction of Diuresis in Patients with Acute Nephrosis

In adults, a dose of 25 g of ALBUMIN (HUMAN) 20% can be infused, administered with an appropriate diuretic once a day for 7 to 10 days.

Hemolytic Disease of the Newborn

In newborns, ALBUMIN (HUMAN) 20% may be administered prior to or during exchange transfusion at a dose of 1 g per kilogram body weight. [ 6 ]

2.2 Administration

Intravenous use only.

Prior to administration, parenteral drug products should be inspected visually for turbidity and discoloration, whenever solution and container permit.

Do not dilute with sterile water for injection.

Do not use solutions of ALBUMIN (HUMAN) 20% which are cloudy or have deposits. Once the infusion container has been opened the contents should be used immediately. Discard the unused portion. Filtration of ALBUMIN (HUMAN) 20% is not required.

The infusion rate should be adjusted according to the individual circumstances and the indication. In plasma exchange during paracentesis, the infusion rate may be higher and should be adjusted to the rate of removal.

If large volumes (> 1500 ml) are administered, the product should be warmed to room temperature before use.

3 DOSAGE FORMS AND STRENGTHS

ALBUMIN (HUMAN) 20% is supplied in

- 10 g in 50 mL infusion bottle
- 20 g in 100 mL infusion bottle

4 CONTRAINDICATIONS

Do not use in individuals who are hypersensitive to albumin preparations, any ingredient in the formulation, or components of the container.

5 WARNINGS AND PRECAUTIONS

5.1 Hypersensitivity

Hypersensitivity or allergic reactions have been observed, and may in some cases progress to severe anaphylaxis. Epinephrine should be available immediately to treat any acute hypersensitivity reaction.

5.2 Hypervolemia/Hemodilution

Hypervolemia may occur if the dosage and rate of infusion are not adjusted to the patient’s volume status. At the first clinical signs of possible cardiovascular overload, e.g., headache, dyspnea, increased blood pressure, jugular venous distention, elevated central venous pressure, pulmonary edema, the infusion should be stopped immediately and the patient reevaluated. Albumin should be used with caution in conditions where hypervolemia and its consequences or hemodilution could represent a special risk for the patient. Examples of such conditions are:

- Decompensated cardiac insufficiency
- Hypertension
- Esophageal varices
- Pulmonary edema
- Hemorrhagic diathesis
- Severe anemia
- Renal and post-renal anuria.

5.3 Electrolyte Imbalance

20-25% Albumin (Human) is relatively low in electrolytes compared to the 4-5% Albumin (Human) solutions. When albumin is given, monitor the electrolyte status of the patient and take appropriate steps to restore or maintain the electrolyte balance.

5.4 Coagulation Abnormalities

If comparatively large volumes are to be replaced, monitoring of coagulation and hematocrit is necessary. Ensure adequate substitution of other blood constituents (coagulation factors, electrolytes, platelets and erythrocytes).

5.5 Laboratory Monitoring

If ALBUMIN (HUMAN) 20% is to be administered, monitor hemodynamic performance regularly; this may include:

- Arterial blood pressure and pulse rate
- Central venous pressure
- Pulmonary artery occlusion pressure
- Urine output
- Electrolytes
- Hematocrit/hemoglobin.

5.6 Application Precautions

ALBUMIN (HUMAN) 20% must not be diluted with sterile water for injection as this may cause hemolysis in recipients.

5.7 Infection Risk from Human Plasma

This product is a derivative of human plasma. Based on effective donor screening and product manufacturing processes it carries an extremely remote risk for transmission of viral diseases. A theoretical risk for transmission of Creutzfeldt-Jakob Disease (CJD) also is considered extremely remote. No cases of transmission of viral diseases or CJD have been identified for ALBUMIN (HUMAN) 20%.

6 ADVERSE REACTIONS

6.1 General

The most serious events are anaphylactic shock, circulatory failure, cardiac failure, and pulmonary edema.

The most common adverse events are anaphylactoid type of reactions.

Adverse reactions for ALBUMIN (HUMAN) 20% normally resolve when the infusion rate is slowed down or the infusion is stopped. In case of severe reactions, the infusion should be stopped and appropriate treatment should be initiated.

6.2 Clinical Studies Experience

No clinical studies were done using ALBUMIN (HUMAN) 20%

6.3 Postmarketing Experience

The following adverse reactions have been identified during post-approval use of ALBUMIN (HUMAN) (any strength). Because these reactions are reported voluntarily from a population of unknown size, it is not always possible to reliably estimate their frequency.

Table 1 Adverse reactions observed for ALBUMIN HUMAN (any strength) during post-marketing phase (in decreasing order of severity)

Observed Adverse Reactions

anaphylactic shock

cardiac failure

loss of consciousness

circulatory failure

hypersensitivity

congestive heart failure

pulmonary edema

dyspnea

hypotension

hypertension

tachycardia

bradycardia

vomiting

urticaria

angioneurotic edema

rash erythematous

confusional state

headache

chills

pyrexia

flushing

nausea

pruritus

hyperhidrosis

No drug interaction studies have been conducted.

7 DRUG INTERACTIONS

No drug interaction studies have been conducted.

8 USE IN SPECIFIC POPULATIONS

8.1 Pregnancy

Risk Summary

There are no data with ALBUMIN (HUMAN) 20% use in pregnant women to determine whether there is a drug-associated risk. Animal reproduction studies have not been conducted with ALBUMIN (HUMAN) 20%. It is not known whether ALBUMIN (HUMAN) 20% can cause fetal harm when administered to a pregnant woman or can affect fertility. ALBUMIN (HUMAN) 20% should be given to a pregnant woman only if clearly needed.

In the U.S. general population, the estimated background risk of major birth defects and miscarriage in clinically recognized pregnancies is 2-4% and 15-20%, respectively.

8.2 Lactation

Risk Summary

There is no information regarding the presence of ALBUMIN (HUMAN) 20% in human milk, the effect on the breastfed infant, or the effects on milk production. The developmental and health benefits of breastfeeding should be considered along with the mother’s clinical need for ALBUMIN (HUMAN) 20% and any potential adverse effects on the breastfed infant from ALBUMIN (HUMAN) 20% or from the underlying maternal condition.

8.4 Pediatric Use

Data on the use of ALBUMIN (HUMAN) 20% in children including premature babies are very limited. The product should be administered to pediatric patients only if needed.

8.5 Geriatric Use

Clinical studies did not include a sufficient number of subjects aged 65 and older to determine whether they respond differently from younger subjects.

11 DESCRIPTION

ALBUMIN (HUMAN) 20% is a sterile, liquid preparation of albumin derived from large pools of human plasma. All units of human plasma used in the manufacture of ALBUMIN (HUMAN) 20% are provided by FDA approved blood establishments only.

The product is manufactured by cold ethanol fractionation followed by ultra- and diafiltration. The manufacturing process includes final container pasteurization and additional bulk pasteurization at 60 +/- 0.5°C for 10 – 11 hours. The ALBUMIN (HUMAN) 20% manufacturing process provides a significant viral reduction in in vitro studies (table 2). These reductions are achieved through a combination of process steps including cold ethanol fractionation and final container pasteurization.

No procedure, however, has been shown to be completely effective in removing viral infectivity from derivatives of human plasma.[see Warnings and Precautions, Infection Risk from Human Plasma (5.7)]

Table 2 In vitro reduction factor during ALBUMIN (HUMAN) 20% manufacturing

PRV:Pseudorabies Virus

SBV: Sindbis Virus

HIV-1:Human Immunodeficiency Virus - 1

Reo 3:Reovirus Type 3

PPV:Porcine Parvovirus

HAV:Hepatitis A Virus

ALBUMIN (HUMAN) 20% is a clear, slightly viscous liquid; it is almost colorless or slightly yellow or green.

The composition of ALBUMIN (HUMAN) 20% is as follows:

Component |  | Quantity/1000 ml
Protein, of which ≥
96% is human albumin |  | 200 g
Sodium |  | 130 – 160 mmol
Potassium |  | ≤ 2 mmol
N-acetyl-DL-tryptophan |  | 0.064 - 0.096 mmol/g protein
Caprylic acid |  | 0.064 - 0.096 mmol/g protein
Water for Injection |  | ad. 1000 ml

ALBUMIN (HUMAN) 20% contains no preservatives and components used in its packaging are latex-free.

12 CLINICAL PHARMACOLOGY

No pharmacokinetic or pharmacodynamic studies with ALBUMIN (HUMAN) 20% have been conducted.

12.1 Mechanism of Action

Albumin is responsible for 75-80% of the colloid osmotic pressure of normal plasma. Albumin stabilizes circulating blood volume and is a carrier of hormones, enzymes, medicinal products and toxins. [ 3 ]

Albumin is a protein with a total extravascular mass of approximately 160 g and an intravascular mass of about 120 g. [ 3 ]

12.2 Pharmacodynamics

The colloid osmotic effect of ALBUMIN (HUMAN) 20% and 25% is approximately 5 times the volume administered. When injected intravenously, it will increase circulating plasma volume by approximately 3.5 times the volume infused within 15 minutes if the patient is adequately hydrated. This extra fluid reduces hemoconcentration and blood viscosity. The degree and duration of volume expansion depends upon the initial blood volume. When treating patients with diminished blood volume, the effect of infused albumin may persist for many hours. The hemodilution lasts for a shorter time when albumin is administered to individuals with normal blood volume. [ 4 ]

13 NONCLINICAL TOXICOLOGY

No non-clinical toxicology studies with ALBUMIN (HUMAN) 20% have been conducted. Human Albumin is a normal constituent of human plasma and acts like physiological albumin.

14 CLINICAL STUDIES

No clinical studies with ALBUMIN (HUMAN) 20% have been conducted.

15 REFERENCES

1. Tullis JL: Albumin 2.Guidelines for Clinical Use. JAMA 1977; 237:460-463
2. Vermeulen LC et al.: A Paradigm for Consensus. Arch. Intern. Med. 1995; 155:373-379
3. Mendez CM, McClain CJ, Marsano LS: Albumin Therapy in Clinical Practice. Nutrition in Clinical Practice 2005; 20: 314-320
4. Janeway, C. A. "Human Serum Albumin: Historical Review" in: Proceedings of the Workshop on Albumin. DHEW Publication No. (NIH) 76-925. Sgouris, J. T. and René A. (eds.), Washington, D.C., U.S. Government Printing Office. 1976, pp 3-21.
5. Martin GS et al.: A randomized, controlled trail of furosemide with or without albumin in hypoproteinemic patients with acute lung injury. Crit. Care Med. 2005; 33: 1681-1687
6. Tsao YC, Yu VY: Albumin in management of neonatal hyperbilirubinaemia. Arch Dis.Child 1972;47:250-256.
7. Practice Committee of the American Society for Reproductive Medicine. Ovarian hyperstimulation syndrome. Fertil.Steril. 2006;86:S178-S183.
8. Aboulghar M, Evers JH, Al Inany H: Intravenous albumin for preventing severe ovarian hyperstimulation syndrome: a Cochrane review. Hum.Reprod. 2002;17:3027-3032.

16 HOW SUPPLIED/STORAGE AND HANDLING

ALBUMIN (HUMAN) 20% is supplied in 10 g in 50 mL or 20 g in 100 mL single use bottles.

NDC Number | Size | Grams protein
68982-633-01 | 50 ml | 10
68982-633-02 | 100 ml | 20

ALBUMIN (HUMAN) 20% may be stored for 36 months at +2°C to + 25°C (36°F to 77°F) from the date of manufacture.

Store protected from light.

Do not freeze.

Do not use after expiration date.

Do not use if turbid.

17 PATIENT COUNSELING INFORMATION

17.1 Information for Patients

This product is usually given in a hospital setting.

Inform patients being treated with Albumin (Human) 20% about the potential risks and benefits with its use [see Adverse Reactions (6)].

Discontinue immediately if allergic symptoms occur (e.g. skin rashes, hives, itching, breathing difficulties, coughing, nausea, vomiting, fall in blood pressure, increased heart rate).

Inform patients that ALBUMIN (HUMAN) 20% is a derivative of human plasma and may contain infectious agents that cause disease (e.g., viruses, and theoretically, CJD agent). Inform patients that the risk that ALBUMIN (HUMAN) 20% may transmit an infectious agent has been reduced by screening plasma donors for prior exposure for certain viruses, by testing the donated plasma for certain virus infections and by inactivating and/or removing certain viruses during manufacturing [see Warnings and Precautions (5.7)].

Manufactured by:

Octapharma Pharmazeutika Produktionsges.m.b.H.

Oberlaaer Strasse 235

A-1100 Vienna, Austria

Octapharma AB

Lars Forssells gata 23

SE- 112 75, Sweden

U.S. License No. 1646

Distributed by:

Octapharma USA Inc.

117 West Century Road

Paramus, NJ 07652

PACKAGE LABEL - PRINCIPAL DISPLAY PANEL

Albumin (Human) 20%

10 g in 50 mL

NDC 68982-633-01

Albumin (Human) 20%

20 g in 100 mL

NDC 68982-633-02